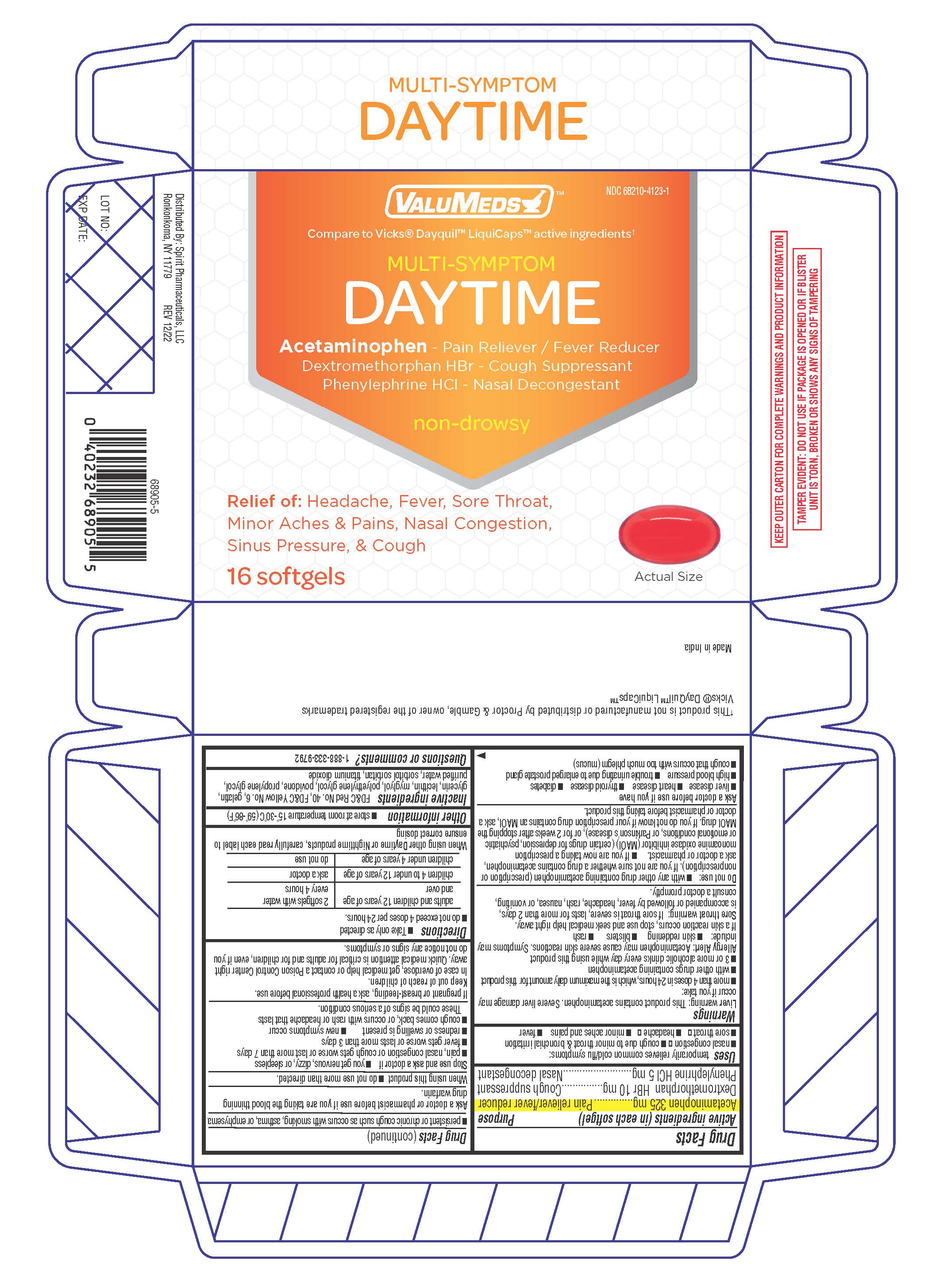 DRUG LABEL: MULTI-SYMPTOM DAYTIME
NDC: 68210-5004 | Form: CAPSULE, LIQUID FILLED
Manufacturer: SPIRIT PHARMACEUTICALS LLC
Category: otc | Type: HUMAN OTC DRUG LABEL
Date: 20241230

ACTIVE INGREDIENTS: ACETAMINOPHEN 325 mg/1 1; DEXTROMETHORPHAN HYDROBROMIDE 10 mg/1 1; PHENYLEPHRINE HYDROCHLORIDE 5 mg/1 1
INACTIVE INGREDIENTS: FD&C RED NO. 40; GELATIN; GLYCERIN; LECITHIN, SOYBEAN; MEDIUM-CHAIN TRIGLYCERIDES; POLYETHYLENE GLYCOL 400; POVIDONE K30; PROPYLENE GLYCOL; WATER; SORBITOL; TITANIUM DIOXIDE; FD&C YELLOW NO. 6

VALUMEDS DAY TIME COLD & FLU MULTI-SYMPTOM RELIEF

Drug Facts

ACTIVE INGREDIENT

Active ingredients (in each softgel) | Purpose
Acetaminophen 325 mg | Pain reliever/fever reducer
Dextromethorphan Hydrobromide 10 mg | Cough suppressant
Phenylephrine HCl 5 mg | Nasal decongestant

Uses

temporarily relieves common cold/flu symptoms:

- nasal congestion
- cough due to minor throat & bronchial irritation
- sore throat
- headache
- minor aches/pains
- fever

Warnings

Liver warning

This product contains acetaminophen. Severe liver damage may occur if you take:

- more than 4 doses in 24 hours, which is the maximum daily amount for this product
- with other drugs containing acetaminophen
- 3 or more alcoholic drinks every day while using this product

Allergy alert:

acetaminophen may cause severe skin reactions. Symptoms may include:

- skin reddening
- blisters
- rash

Sore throat warning:

If sore throat is severe, lasts for more than 2 days, occurs with or is followed by fever, headache, rash, nausea, or vomiting, see a doctor promptly.

Do not use:

- with any other drug containing acetaminophen (prescription or nonprescription). If you are not sure whether a drug contains acetaminophen, ask a doctor or pharmacist.
- If you are now taking a prescription monoamine oxidase inhibitor (MAOI) (certain drugs for depression, psychiatric or emotional conditions, or Parkinson's disease), or for 2 weeks after stopping the MAOI drug. If you do not know if your prescription drug contains an MAOI, ask a doctor or pharmacist before taking this product.

Ask a doctor before use if you have

- liver disease
- heart disease
- thyroid disease
- diabetes
- high blood pressure
- trouble urinating due to enlarged prostate gland
- cough that occurs with too much phlegm (mucus)
- persistent or chronic cough as occurs with smoking, asthma, or emphysema

Ask a doctor or pharmacist before use if you are taking the blood-thinning drug Warfarin.

When using this product

- do not use more than directed.

Stop use and ask a doctor if

- you get nervous, dizzy, or sleepless
- pain, nasal congestion or cough gets worse or last more than 7 days
- fever gets worse or lasts more than 3 days
- redness or swelling is present
- new symptoms occur
- cough comes back, or occurs with rash or headache that lasts

These could be signs of a serious condition.

PREGNANCY OR BREAST FEEDING

If pregnant or breast-feeding, ask a health professional before use.

Keep out of reach of children.

Overdose warning

Taking more than directed can cause serious health problems. In case of overdose, get medical help or contact a Poison Control Center right away. Quick medical attention is critical for adults and for children, even if you do not notice any signs or symptoms.

Directions

- Take only as directed—see Overdose warning.
- do not exceed 4 doses per 24 hours.

adults and children 12 years of age and over | swallow 2 softgels with water every 4 hours
children 4 to under 12 years of age | ask a doctor
children under 4 years of age | do not use

If taking Daytime and Nighttime softgels carefully read each label to insure correct dosing

Other information

- store at room temperature 15°-30°C (59°-86°F) and avoid excessive heat
- this product does not contain phenylpropanolamine

Inactive ingredients

FD&C Red No. 40, FD&C Yellow No. 6, gelatin, glycerin, lecithin, myglyol, polyethylene glycol, povidone, propylene glycol, purified water, sorbitol sorbitan, titanium dioxide

Questions or comments?

1-888-333-9792

THIS PRODUCT IS PACKAGED IN A CHILD RESISTANT AND TAMPER EVIDENT PACKAGE. USE ONLY IF BLISTERS ARE INTACT.

PRINCIPAL DISPLAY PANEL

SEE NEW WARNINGS INFORMATION

COMPARE TO ACTIVE INGREDIENTS IN
VICKS® DAYQUIL®*

VALUMEDS™

NON-DROWSY

DAY TIME

COLD & FLU MULTI-SYMPTOM RELIEF

ACETAMINOPHEN, DEXTROMETHORPHAN HBr, PHENYLEPHRINE HCl

Pain Reliever

- Fever Reducer
- Cough Suppressant
- Nasal Decongestant

16 SOFTGELS

Liquid filled capsules